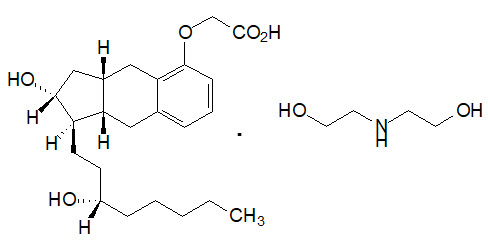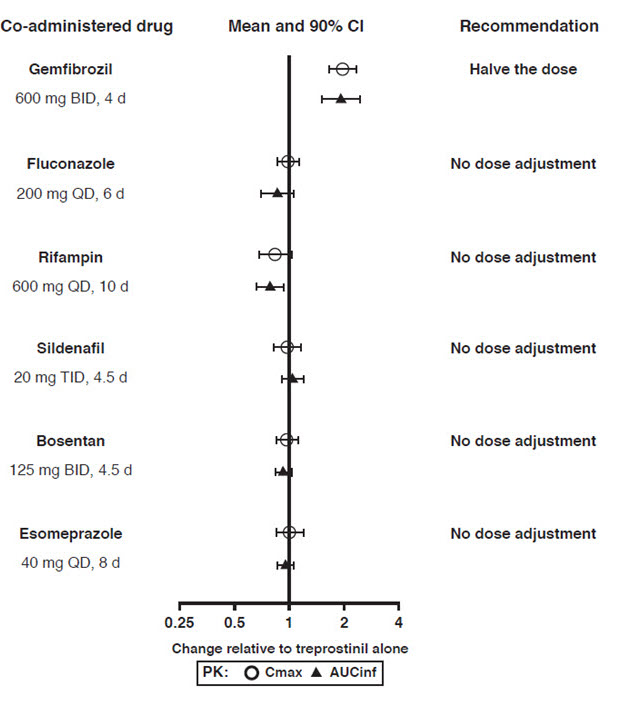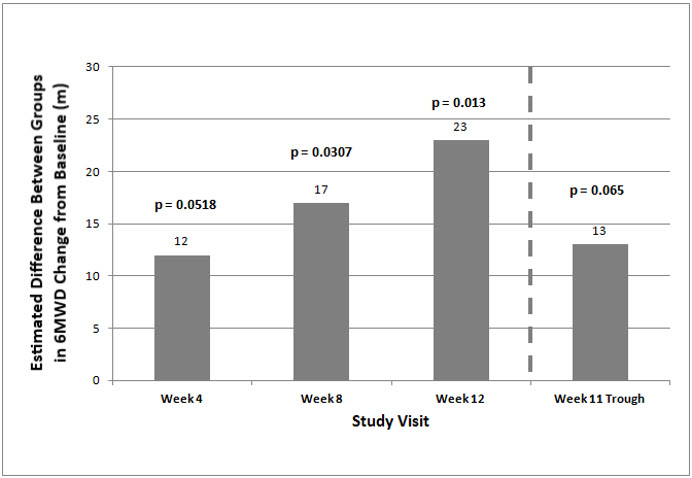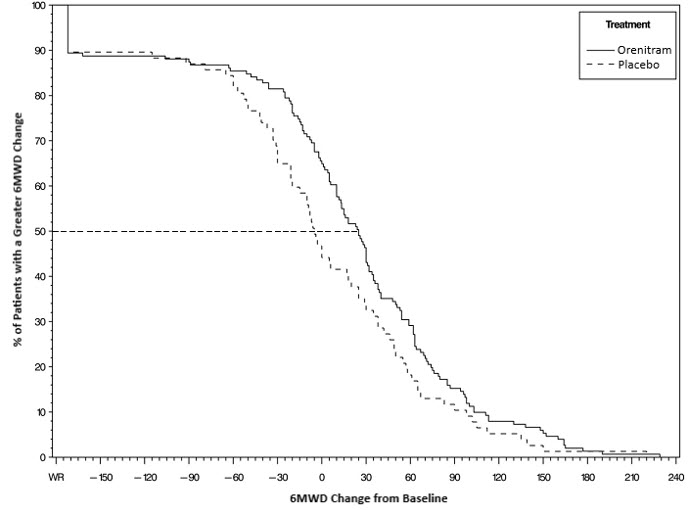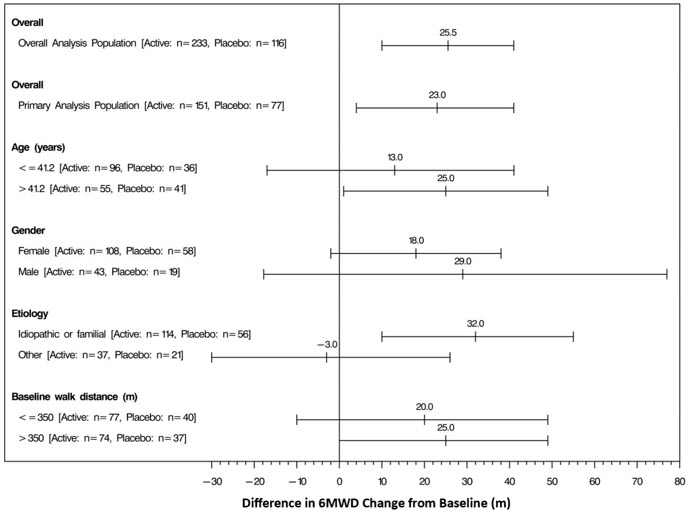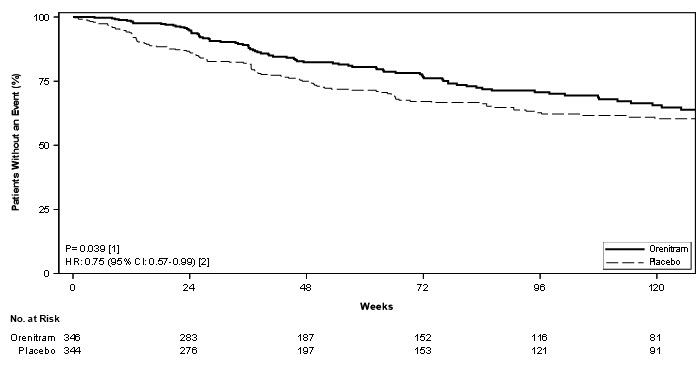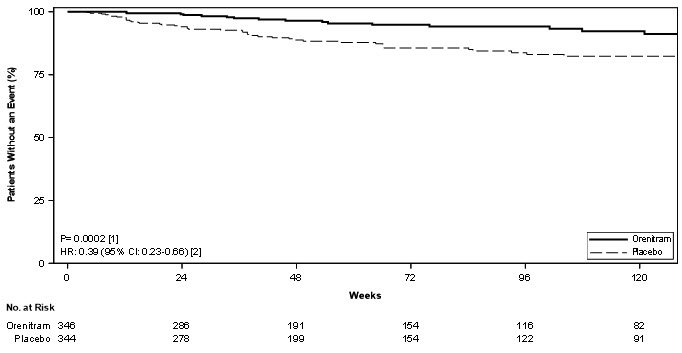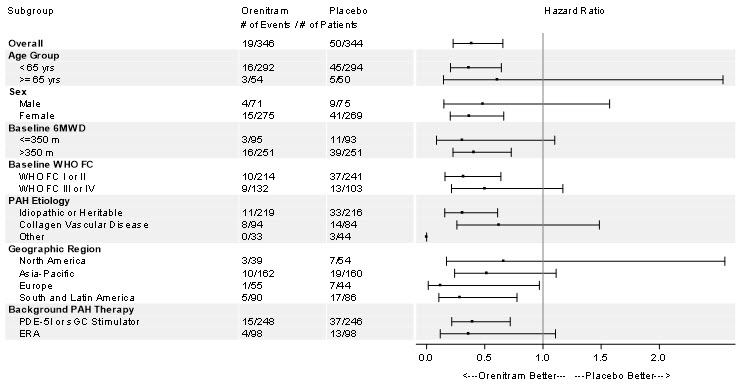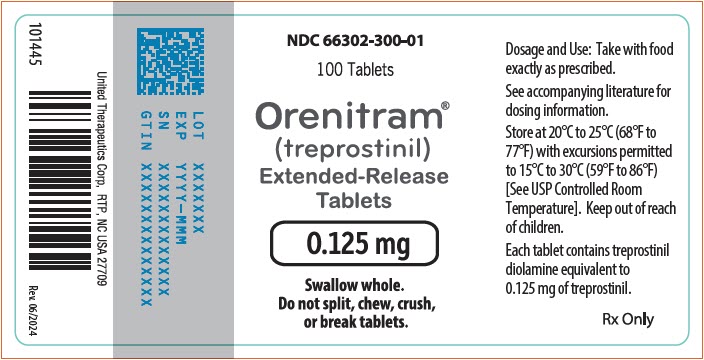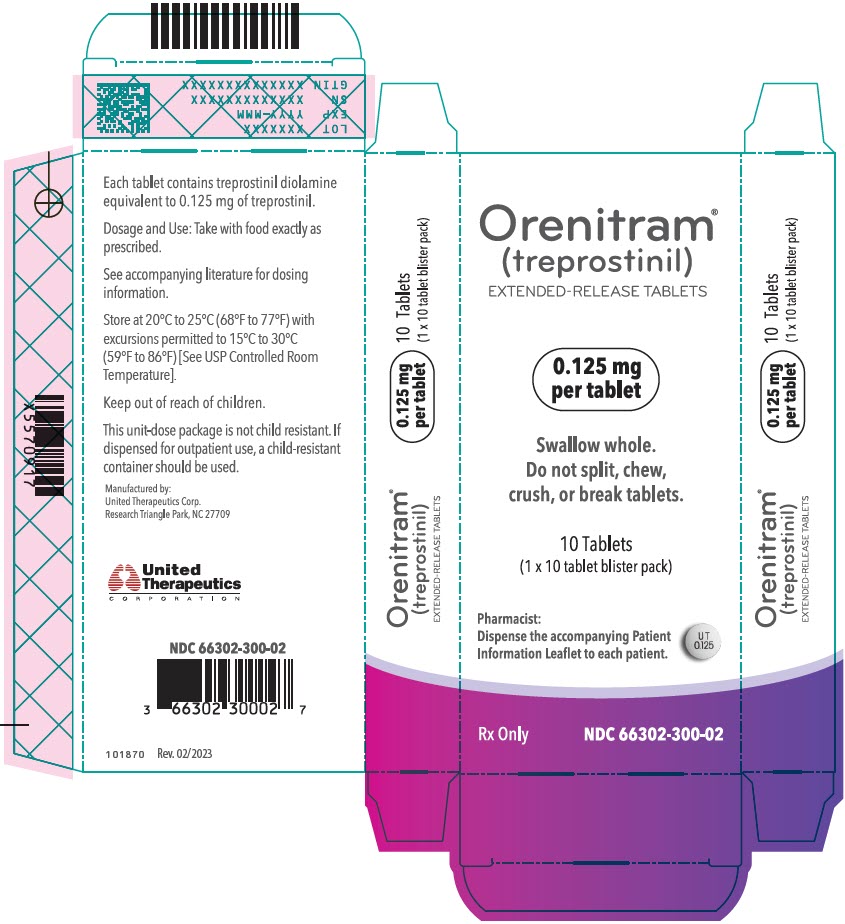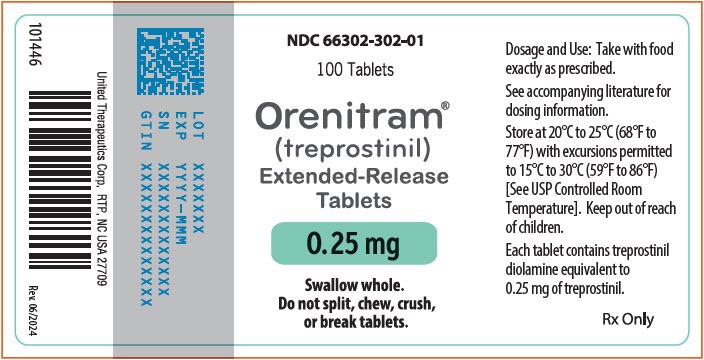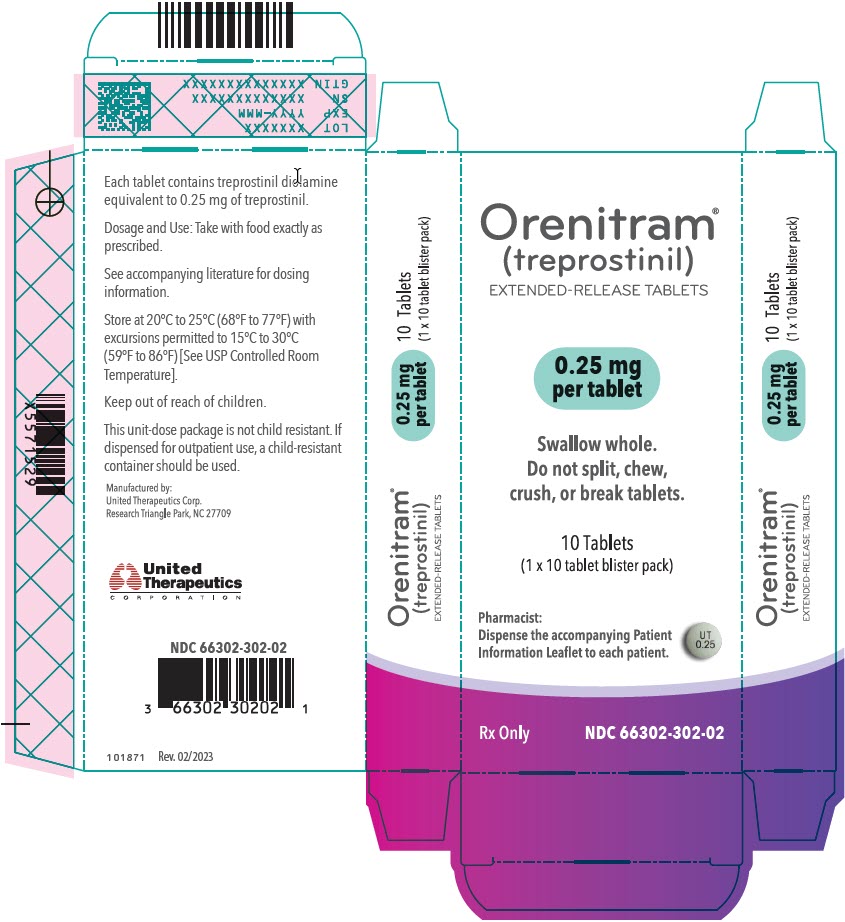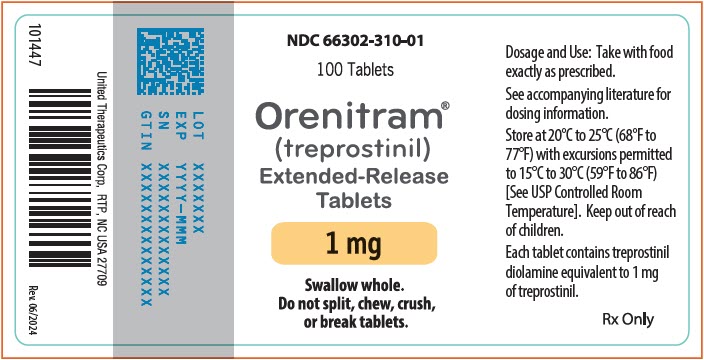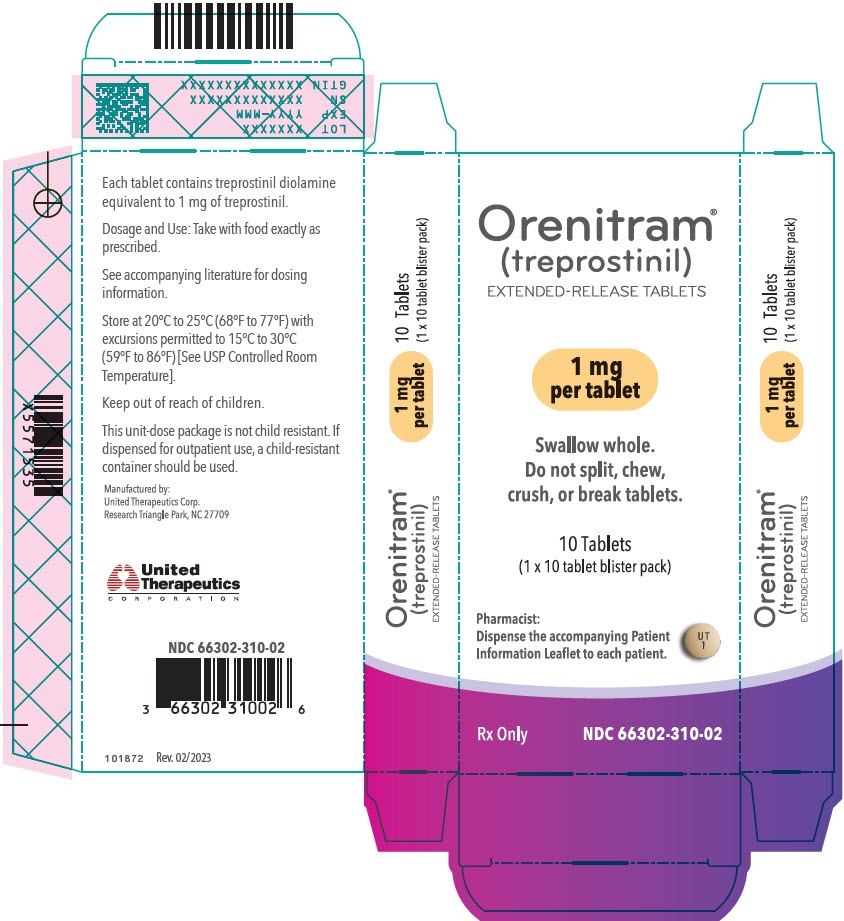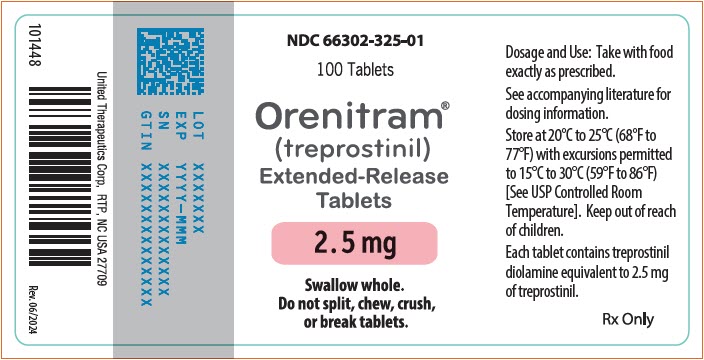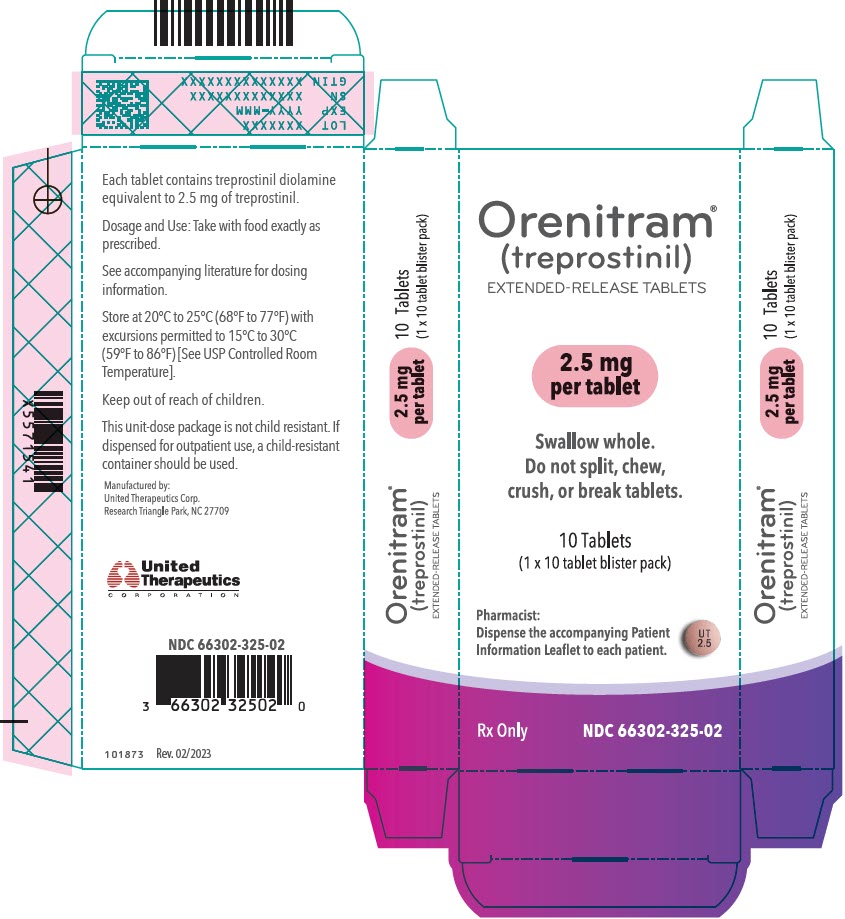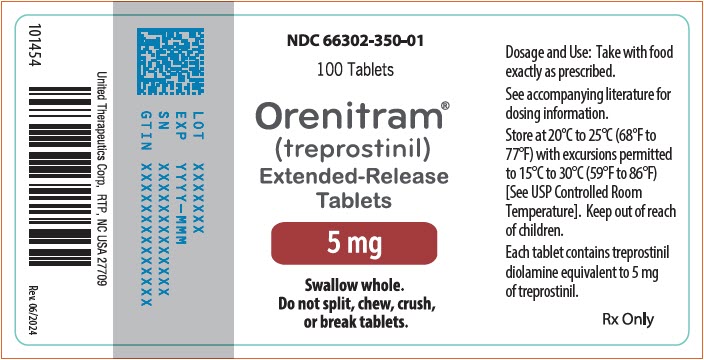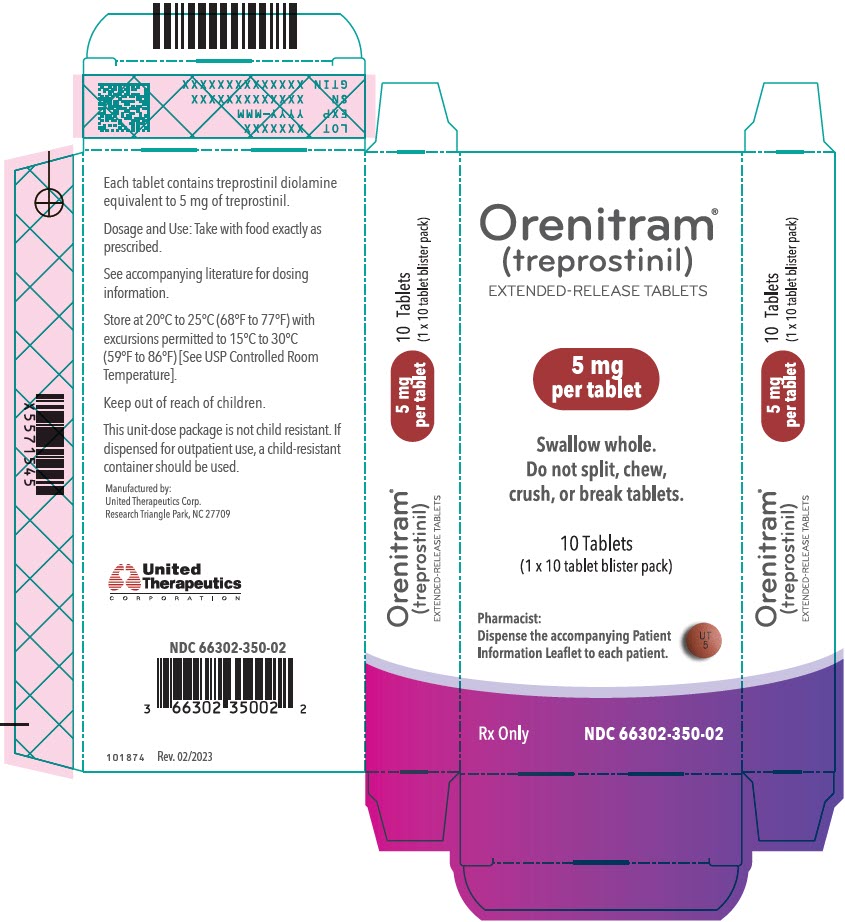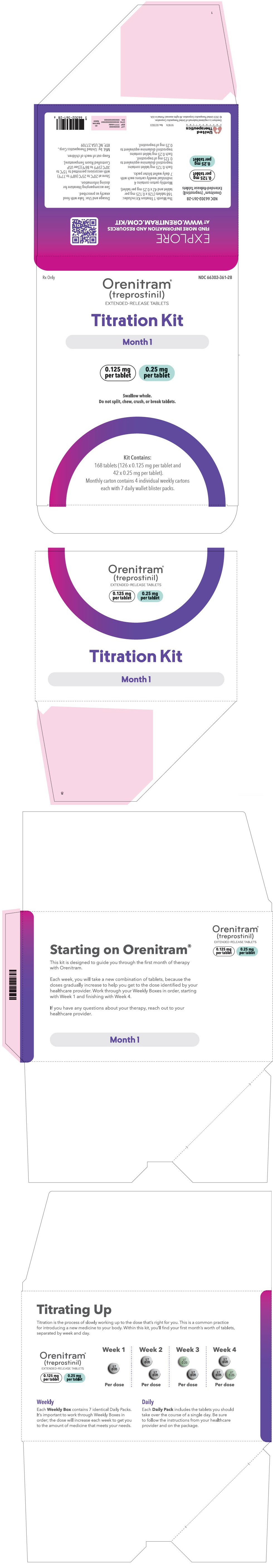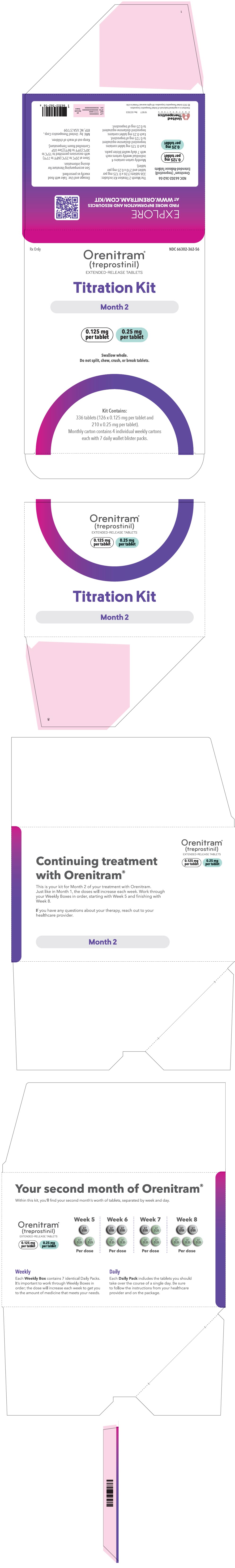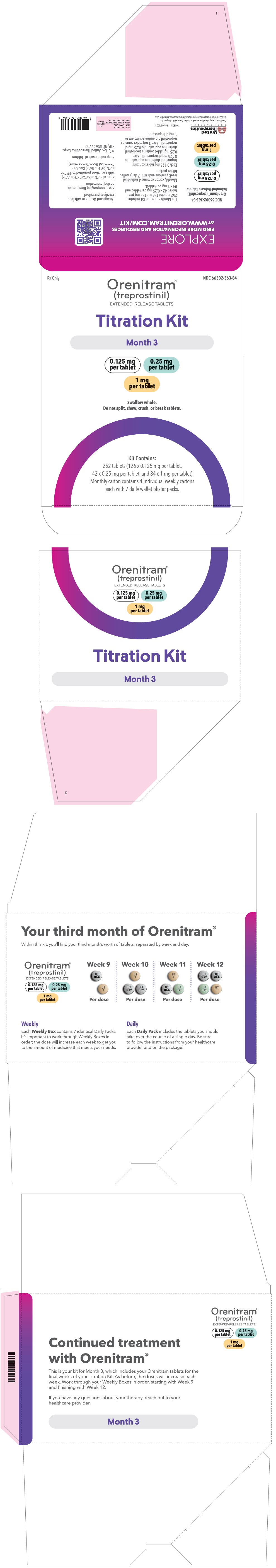 DRUG LABEL: Orenitram
NDC: 66302-300 | Form: TABLET, EXTENDED RELEASE
Manufacturer: United Therapeutics Corporation
Category: prescription | Type: HUMAN PRESCRIPTION DRUG LABEL
Date: 20241120

ACTIVE INGREDIENTS: treprostinil 0.125 mg/1 1
INACTIVE INGREDIENTS: Xylitol; Maltodextrin; Sodium Lauryl Sulfate; Magnesium Stearate; Cellulose Acetate; Triethyl Citrate; Polyvinyl alcohol, unspecified; Titanium Dioxide; Polyethylene Glycol 3350; Talc; Shellac; Ferrosoferric Oxide; BUTYL ALCOHOL; Alcohol; Isopropyl Alcohol; Propylene Glycol

HIGHLIGHTS OF PRESCRIBING INFORMATION

These highlights do not include all the information needed to use ORENITRAM safely and effectively. See Full Prescribing Information for ORENITRAM.
ORENITRAM® (treprostinil) extended-release tablets, for oral use
Initial U.S. Approval: 2002

RECENT MAJOR CHANGES

Dosage and Administration (2.1) | 08/2023

1 INDICATIONS AND USAGE

Orenitram is a prostacyclin mimetic indicated for the treatment of pulmonary arterial hypertension (PAH) (WHO Group 1):

- To delay disease progression and to improve exercise capacity. The studies that established effectiveness included predominately patients with WHO functional class II-III symptoms and etiologies of idiopathic or heritable PAH (66%) or PAH associated with connective tissue disease (26%). (1.1)

2 DOSAGE AND ADMINISTRATION

- Give with food. Swallow tablets whole; use only intact tablets. (2.1)
- Starting dose: 0.125 mg TID or 0.25 mg BID. (2.1)
- Titrate by 0.125 mg TID or by 0.25 mg or 0.5 mg BID, not more frequently than every 3 to 4 days as tolerated. The maximum daily dose is 120 mg. (2.1)
- If transitioning from intravenous (IV) or subcutaneous (SC) Remodulin®, the Orenitram dose should be increased while simultaneously decreasing the IV/SC infusion rate. (2.2)
- Mild hepatic impairment (Child Pugh Class A): Initiate at 0.125 mg BID. Increment at 0.125 mg BID not more frequently than every 3 to 4 days. (2.3)
- Avoid use in patients with moderate hepatic impairment. (2.3)

3 DOSAGE FORMS AND STRENGTHS

Extended-Release Tablets: 0.125 mg, 0.25 mg, 1 mg, 2.5 mg, and 5 mg. (3)

4 CONTRAINDICATIONS

- Severe hepatic impairment (Child Pugh Class C). (4)

5 WARNINGS AND PRECAUTIONS

- Do not abruptly discontinue dosing. (2.5, 5.1)
- In patients with diverticulosis, Orenitram tablets can become lodged in a diverticulum. (5.2)

6 ADVERSE REACTIONS

Most common adverse reactions (incidence >10%) reported in clinical studies in patients treated with Orenitram compared with placebo are headache, diarrhea, nausea, vomiting, jaw pain, and flushing. (6.1)

To report SUSPECTED ADVERSE REACTIONS, contact United Therapeutics Corp. at 1-866-458-6479 or FDA at 1-800-FDA-1088 or www.fda.gov/medwatch.

7 DRUG INTERACTIONS

- When co-administered with strong CYP2C8 inhibitors the initial dose is 0.125 mg BID with 0.125 mg BID dose increments not more frequently than every 3 to 4 days. (2.4, 7.1)

FULL PRESCRIBING INFORMATION

1 INDICATIONS AND USAGE

1.1 Pulmonary Arterial Hypertension

Orenitram is indicated for the treatment of pulmonary arterial hypertension (PAH) (WHO Group 1) to delay disease progression and to improve exercise capacity.

The studies that established effectiveness included predominately patients with WHO functional class II-III symptoms and etiologies of idiopathic or heritable PAH (66%) or PAH associated with connective tissue disease (26%).

2 DOSAGE AND ADMINISTRATION

2.1 Recommended Dosing

Take Orenitram with food. Swallow Orenitram tablets whole; do not crush, split, or chew.

The recommended starting dose of Orenitram is 0.125 mg three times daily (TID) with food, taken approximately 8 hours apart or 0.25 mg twice daily (BID) with food, taken approximately 12 hours apart.

Titrate by 0.125 mg TID or 0.25 or 0.5 mg BID not more frequently than every 3 to 4 days. Increase the dose to the highest tolerated dose. The recommended maximum daily dose is 120 mg.

If dose increments are not tolerated, consider titrating slower. If intolerable pharmacologic effects occur, decrease the dose in increments of 0.125 mg TID or 0.25 mg BID. Avoid abrupt discontinuation [see Warnings and Precautions (5.1)].

2.2 Transitioning from Subcutaneous or Intravenous Routes of Administration of Treprostinil

Decrease the dose of Remodulin while simultaneously increasing the dose of Orenitram. The dose of Remodulin can be reduced up to 30 ng/kg/min per day and the dose of Orenitram simultaneously increased up to 6 mg per day (2 mg TID) if tolerated. The following equation can be used to estimate a target total daily dose of Orenitram in mg using a patient's dose of intravenous (IV)/subcutaneous (SC) treprostinil (in ng/kg/min) and weight (in kg).

Orenitram total daily dose (mg) = 0.0072 × Remodulin dose (ng/kg/min) × weight (kg)

2.3 Dose Adjustment in Patients with Hepatic Impairment

In patients with mild hepatic impairment (Child Pugh Class A) start at 0.125 mg BID with 0.125 mg BID dose increments not more frequently than every 3 to 4 days. Avoid use of Orenitram in patients with moderate hepatic impairment (Child Pugh Class B). Orenitram is contraindicated in patients with severe hepatic impairment (Child Pugh Class C) due to increases in systemic exposure [see Contraindications (4), Use in Specific Populations (8.6), and Clinical Pharmacology (12.3)].

2.4 Dose Adjustment for Use with CYP2C8 Inhibitors

When co-administered with strong CYP2C8 inhibitors (e.g., gemfibrozil) the initial dose is 0.125 mg BID with 0.125 mg BID dose increments not more frequently than every 3 to 4 days.

2.5 Interruptions and Discontinuation

If a dose of medication is missed, the patient should take the missed dose as soon as possible, with food. If a patient misses two or more doses, restart at a lower dose and re-titrate.

In the event of a planned short-term treatment interruption for patients unable to take oral medications, consider a temporary infusion of subcutaneous or intravenous treprostinil. To calculate the total daily dose (mg) of treprostinil for the parenteral route use the following equation:

Remodulin (ng/kg/min) = | 139 × Orenitram total daily dose (mg)
 | weight (kg)

When discontinuing Orenitram, reduce the dose in steps of 0.5 to 1 mg per day [see Warnings and Precautions (5.1)].

3 DOSAGE FORMS AND STRENGTHS

Orenitram (treprostinil) extended-release tablets are available in the following five strengths:

- 0.125 mg [White tablet imprinted with UT 0.125]
- 0.25 mg [Green tablet imprinted with UT 0.25]
- 1 mg [Yellow tablet imprinted with UT 1]
- 2.5 mg [Pink tablet imprinted with UT 2.5]
- 5 mg [Red tablet imprinted with UT 5]

4 CONTRAINDICATIONS

Severe hepatic impairment (Child Pugh Class C) [see Use In Specific Populations (8.6) and Clinical Pharmacology (12.3)].

5 WARNINGS AND PRECAUTIONS

5.1 Worsening PAH Symptoms upon Abrupt Withdrawal

Abrupt discontinuation or sudden large reductions in dosage of Orenitram may result in worsening of PAH symptoms.

5.2 Use in Patients with Blind-end Pouches

The tablet shell does not dissolve. In patients with diverticulosis, Orenitram tablets can lodge in a diverticulum.

6 ADVERSE REACTIONS

6.1 Clinical Trials Experience

Because clinical trials are conducted under widely varying conditions, adverse reaction rates observed in the clinical trials of a drug cannot be directly compared to rates in the clinical trials of another drug and may not reflect the rates observed in clinical practice.

In a 12-week, placebo-controlled, monotherapy study (Study 1; WHO Group 1; functional class II-III), and an event-driven, placebo-controlled, combination therapy study (Study 4; WHO Group 1; functional class I-III), the most commonly reported adverse reactions that occurred in patients receiving Orenitram included: headache, diarrhea, nausea, and flushing.

Orenitram patients in Study 1 (N=151) had access to 0.25 mg tablets at randomization. Approximately 91% of such patients in Study 1 experienced an adverse reaction, but only 4% discontinued therapy for an adverse reaction (compared to 3% receiving placebo). Study 4 enrolled a total of 690 patients, 346 received Orenitram and 344 received placebo. Overall, 19% of patients treated with Orenitram discontinued treatment in Study 4 due to an adverse event (compared to 4% of patients receiving placebo). The exposure to Orenitram in Study 4 was up to 5.1 years with a median duration of exposure of 1.2 years. Table 1 summarizes adverse events with rates at least 5% higher on Orenitram therapy than on placebo that were reported in either Study 1 or 4.

Table 1: Adverse Events with Rates at Least 5% Higher on Orenitram Therapy than on Placebo in Either Study 1 or Study 4
Reaction | Study 1 N=228 [Includes all subjects in the Primary Analysis Population] |  | Study 4 N=690
Reaction | Orenitram n=151 | Placebo n=77 | Orenitram n=346 | Placebo n=344
Headache | 63% | 19% | 75% | 35%
Diarrhea | 30% | 16% | 69% | 29%
Nausea | 30% | 18% | 40% | 23%
Vomiting | 17% | 16% | 36% | 10%
Flushing | 15% | 6% | 45% | 8%
Pain in jaw | 11% | 4% | 18% | 3%
Pain in extremity | 14% | 8% | 18% | 9%
Hypokalemia | 9% | 3% | 4% | 3%
Abdominal discomfort | 6% | 0% | 8% | 4%
Upper abdominal pain | 5% | 3% | 12% | 5%

Orenitram was studied in a long-term, open-label, extension study in which 824 patients were dosed for a mean duration of approximately 2 years. About 70% of patients continued treatment with Orenitram for at least a year. The mean dose was 4.2 mg BID at one year. The adverse reactions were similar to those observed in the placebo-controlled trials.

The safety of Orenitram was also evaluated in an open-label study transitioning patients from Remodulin. The safety profile during this study was similar to that observed in the three pivotal studies.

6.2 Post-Marketing Experience

The following adverse reactions have been identified during postapproval use of Orenitram: dizziness, dyspepsia, vomiting, myalgia, and arthralgia. Because these reactions are reported voluntarily from a population of uncertain size, it is not always possible to reliably estimate their frequency or establish a causal relationship to drug exposure.

7 DRUG INTERACTIONS

7.1 Effect of CYP2C8 Inhibitors on Treprostinil

Co-administration of Orenitram and the CYP2C8 enzyme inhibitor gemfibrozil in healthy adult volunteers increases exposure to treprostinil. Reduce the starting dose of Orenitram to 0.125 mg BID and use 0.125 mg BID increments not more frequently than every 3 to 4 days [see Dosage and Administration (2.4) and Clinical Pharmacology (12.3)].

8 USE IN SPECIFIC POPULATIONS

8.1 Pregnancy

Risk Summary

Limited published data from case reports with Orenitram use in pregnant women are not sufficient to assess for a drug-associated risk of major birth defects, miscarriage, or adverse maternal or fetal outcomes. There are risks to the mother and the fetus associated with pulmonary arterial hypertension (see Clinical Considerations). Animal reproductive studies with treprostinil diolamine administered orally have shown an adverse effect on the fetus. In rats, administration of treprostinil to pregnant rats during the period of organogenesis at doses ≥10 mg/kg/day (approximately 15 times the human exposure at the dose of 3.5 mg BID on an AUC basis) resulted in decreased pregnancy rate, increased post-implantation loss, and decreased fetal viability and growth. In rabbits, teratogenicity and decreased fetal viability and growth were observed at doses ≥1.5 mg/kg/day (approximately 7 times the human exposure at the dose of 3.5 mg BID on an AUC basis) (see Animal Data).

The estimated background risk of major birth defects and miscarriage for the indicated populations is unknown. All pregnancies have a background risk of birth defect, loss, or other adverse outcomes. In the U.S. general population, the estimated background risk of major birth defects and miscarriage in clinically recognized pregnancies is 2 to 4% and 15 to 20%, respectively.

Clinical Considerations

Disease-associated maternal and embryo-fetal risk

Pulmonary arterial hypertension in pregnancy increases the risk of maternal heart failure, stroke and death, preterm delivery, low birth weight, and stillbirth.

Data

Animal Data

In pregnant rats, reversible, dose-dependent decreases in body weight gain and food consumption were observed during the first four days of dosing in animals administered 10, 20, and 30 mg/kg/day treprostinil diolamine. In a dose range-finding study, there was a 17% decrease in the pregnancy rate in the animals administered 20 and 30 mg/kg/day. One dam in each of the 20 and 30 mg/kg/day had litters with no viable fetuses. In the definitive study (0, 5, 10, and 20 mg/kg/day), there were four treatment-related deaths, and a 32% decrease in the pregnancy rate for rats administered 20 mg/kg/day. There was an 8% decrease in the pregnancy rate in the animals administered 10 mg/kg/day. Across both studies, an increase in post-implantation loss was observed in animals administered 10 to 30 mg/kg/day, and a significant decrease in the mean number of live births was seen at dose levels ≥10 mg/kg/day. The no observed adverse effect level was 5 mg/kg/day (maternal, fetal viability and growth), and 20 mg/kg/day (teratogenicity), the highest dose tested in the definitive study. The exposures at 5 and 20 mg/kg/day doses represent 8 and 33 times, respectively, the human exposure at the dose of 3.5 mg BID on an AUC basis.

For F1 progeny, a decreased copulation index was observed at the 5 and 10 mg/kg/day treprostinil diolamine dose levels in rats. The no observed effect levels for physical development, reflex development, exploratory behavior, learning and memory, and sexual maturation was 10 mg/kg/day. The no observed effect level for F1 progeny general development (based on body weight) was 10 mg/kg/day for females and ≤2.5 mg/kg/day for males; the no observed effect level for F1 reproductive performance was 2.5 mg/kg/day (approximately 4 times the human exposure at the dose of 3.5 mg BID on an AUC basis).

In pregnant rabbits, the primary maternal adverse effect was gastrointestinal disturbance; dose-dependent decreases in mean body weight, body weight gain, and food consumption were observed. During the post-dose phase, the effect was reversed. In a dose range-finding study, there was a 17% decrease in the pregnancy rate for animals administered 4 mg/kg/day. A dose-dependent increase in post-implantation loss was observed. Two dams administered 4 mg/kg/day had litters with no viable fetuses; the mean fetal weight was slightly decreased in animals administered 4 mg/kg/day. In the definitive study, mean fetal weights were significantly decreased in animals administered 0.5 to 3 mg/kg/day of treprostinil diolamine. At doses of 1.5 and 3 mg/kg/day, external fetal and soft tissue malformations were observed in a few fetuses, and the total fetal skeletal malformations were significantly increased. The no observed adverse effect level was less than 0.5 mg/kg/day (maternal), 1.5 mg/kg/day (fetal viability and growth), and 0.5 mg/kg/day (teratogenicity). The 0.5 mg/kg/day dose represents about 3 times the human exposure at the dose of 3.5 mg BID on an AUC basis.

8.2 Lactation

Risk Summary

There are no data on the presence of treprostinil in human milk, the effects on the breastfed infant, or the effects on milk production.

8.4 Pediatric Use

Safety and effectiveness in pediatric patients have not been established.

8.5 Geriatric Use

Use of Orenitram in patients aged 65 years and over demonstrated slightly higher absolute and relative adverse event rates compared to younger patients. In general, dose selection for an elderly patient should be cautious, reflecting the greater frequency of decreased hepatic or cardiac function, and of concomitant disease or other drug therapy.

8.6 Patients with Hepatic Impairment

There is a marked increase in the systemic exposure to treprostinil in hepatically impaired patients [see Dosage and Administration (2.3), Contraindications (4), and Clinical Pharmacology (12.3)].

8.7 Patients with Renal Impairment

No dose adjustments are required in patients with renal impairment. Orenitram is not removed by dialysis [see Clinical Pharmacology (12.3)].

10 OVERDOSAGE

Signs and symptoms of overdose with Orenitram during clinical trials reflect its dose-limiting pharmacologic effects and include severe headache, nausea, vomiting, diarrhea, and hypotension. Treat supportively.

11 DESCRIPTION

Orenitram is an extended-release osmotic tablet for oral administration. Orenitram is formulated as the diolamine salt of treprostinil, a tricyclic benzindene analogue of prostacyclin. The chemical name is Acetic acid, 2-[[(1R,2R,3aS,9aS)-2,3,3a,4,9,9a-hexahydro-2-hydroxy-1-[(3S)-3-hydroxyoctyl]-1H-benz[f]inden-5-yl]oxy]-, complexed with 2,2'-iminobis[ethanol] (1:1). The molecular formula is C23H34O5∙C4H11NO2, the molecular weight is 495.65, and it has the following structural formula:

Orenitram tablets are formulated in five strengths, which contain 0.125 mg of treprostinil (equivalent to 0.159 mg treprostinil diolamine), 0.25 mg of treprostinil (equivalent to 0.317 mg treprostinil diolamine), 1 mg of treprostinil (equivalent to 1.27 mg treprostinil diolamine), 2.5 mg of treprostinil (equivalent to 3.17 mg treprostinil diolamine), or 5 mg of treprostinil (equivalent to 6.35 mg treprostinil diolamine). The formulations also contain xylitol, maltodextrin, sodium lauryl sulfate, magnesium stearate, cellulose acetate, triethyl citrate, polyvinyl alcohol, titanium dioxide, polyethylene glycol, and talc. In addition, tablets may contain colorants FD&C Blue #2, iron oxide yellow, and iron oxide red. The imprint ink contains shellac glaze, ethanol, isopropyl alcohol USP, iron oxide black, n-butyl alcohol, and propylene glycol.

Orenitram is designed to release treprostinil at a near zero-order rate using an osmotic tablet technology. The tablet core is coated with a semi-permeable membrane and has a laser-drilled aperture through the membrane. Upon contact with water (e.g., after ingestion), the core tablet absorbs water through the semi-permeable membrane. The water dissolves the water-soluble treprostinil diolamine and the water-soluble osmotic excipients, which creates hydrostatic pressure within the membrane, eventually forcing the drug across the membrane at a controlled rate.

12 CLINICAL PHARMACOLOGY

12.1 Mechanism of Action

The major pharmacologic actions of treprostinil are direct vasodilation of pulmonary and systemic arterial vascular beds, inhibition of platelet aggregation, and inhibition of smooth muscle cell proliferation.

12.2 Pharmacodynamics

In a clinical trial of 240 healthy adult volunteers, single doses of inhaled treprostinil 54 µg (the target clinical dose) and 84 µg (supratherapeutic inhalation dose) prolonged the corrected QTc interval by approximately 10 msec. The QTc effect dissipated rapidly as the concentration of treprostinil decreased. Orenitram has not been evaluated in a thorough QTc study.

12.3 Pharmacokinetics

In patients with PAH, pharmacokinetics of treprostinil is dose-proportional for systemic exposure (AUC0-t) over the dose range from 0.5 to 15 mg BID. Upon repeat administration with a BID regimen, the accumulation in the systemic exposures to treprostinil is minimal and results in a peak-to-trough ratio of approximately 7. However, a TID regimen will reduce the peak-to-trough fluctuations to approximately 2.5 for the same total daily dose.

Absorption

The absolute oral bioavailability of Orenitram is approximately 17%. Maximum treprostinil concentrations occur between approximately 4 and 6 hours following Orenitram administration. Time to reach steady-state concentrations for both BID and TID regimens is approximately 1 to 2 days.

The absorption of Orenitram is affected by food. The AUCinf of treprostinil was increased by 49% and the Cmax was increased by an average of 13% when Orenitram was administered following a high-fat, high-calorie meal compared to fasting conditions in healthy volunteers. The relative bioavailability of treprostinil following oral administration of Orenitram 1 mg is not significantly altered by meal types ranging from 250 to 500 calories in healthy volunteers.

When Orenitram 1 mg was administered with alcohol at 0.5 mg/kg or the equivalent of 3 servings (at the same time, or ± 1 hour relative to alcohol consumption), there was no significant change (10% to 20% increase) in the exposure to treprostinil compared to Orenitram administered alone.

Distribution

The treprostinil component of Orenitram is highly bound to human plasma proteins, approximately 96% over a treprostinil concentration range of 0.01 to 10 µg/mL.

Metabolism and Excretion

In a study conducted in healthy volunteers using [^14C] treprostinil, treprostinil was extensively metabolized on the side chain of the molecule via oxidation, oxidative cleavage, dehydration, and glucuronic acid conjugation. Treprostinil is primarily metabolized by CYP2C8 and to a lesser extent by CYP2C9. No new major metabolites are found upon oral administration compared to parenteral administration of treprostinil. Only 1.13% and 0.19% is excreted as unchanged parent drug in the feces and urine, respectively. Based on in vitro studies, treprostinil does not inhibit or induce major CYP enzymes [see Drug Interactions (7.1)].

Specific Populations

Hepatic Impairment: In subjects with mild (n=8) hepatic impairment, administration of a single 1 mg dose of Orenitram resulted in a mean Cmax and an AUC0-inf that were 1.6- and 2.1-fold values seen in healthy subjects, respectively. With moderate impairment (n=8), the corresponding ratios were 4.0- and 4.8-fold, and with severe impairment (n=6), they were 4.8- and 7.6-fold [see Dosage and Administration (2.3), Contraindications (4), and Use in Specific Populations (8.6)].

Renal Impairment: In patients with severe renal impairment requiring dialysis (n=8), administration of a single 1 mg dose of Orenitram pre- and post-dialysis resulted in an AUC0-inf that was not significantly altered compared to healthy subjects.

Drug Interactions

Results of drug interaction studies are shown in Figure 1. Only for the strong CYP2C8 inhibitor does the interaction affect dosing [see Dosage and Administration (2.4)].

Figure 1: Impact of Co-Administered Drugs on the Systemic Exposure of Treprostinil 1 mg Compared to Orenitram Administered Alone

Warfarin: A drug interaction study was carried out with Remodulin co-administered with warfarin (25 mg/day) in healthy volunteers. There was no clinically significant effect of either medication on the pharmacokinetics of treprostinil. Additionally, treprostinil did not affect the pharmacokinetics or pharmacodynamics of warfarin. The pharmacokinetics of R- and S-warfarin and the international normalized ratio (INR) in healthy subjects given a single 25 mg dose of warfarin were unaffected by continuous subcutaneous infusion of treprostinil at an infusion rate of 10 ng/kg/min.

13 NONCLINICAL TOXICOLOGY

13.1 Carcinogenesis, Mutagenesis, Impairment of Fertility

Treprostinil diolamine did not demonstrate any carcinogenic effects in mouse or rat carcinogenicity studies. Oral administration of treprostinil diolamine to Tg.rasH2 mice at 0, 5, 10, and 20 mg/kg/day in males and 0, 3, 7.5, and 15 mg/kg/day in females daily for 26 weeks did not significantly increase the incidence of tumors. Oral administration of treprostinil diolamine to Sprague Dawley rats at 0, 1, 3, and 10 mg/kg/day daily for 104 weeks did not significantly increase the incidence of tumors. The exposures obtained at the highest dose levels used in males and females are about 13- and 18-fold, respectively, the human exposure at the dose of 3.5 mg BID on an AUC basis.

In vitro genotoxicity studies with high doses of treprostinil did not demonstrate any mutagenic or clastogenic effects. Treprostinil diolamine was tested in vivo in a rat micronucleus assay and did not induce an increased incidence of micronucleated polychromatic erythrocytes.

In rats, treatment with treprostinil diolamine had no effect on reproductive performance or sperm motility at doses up to 10 mg/kg/day. The exposures at this dose level are about 6- (male) to 11- (female) fold the human exposure at the dose of 3.5 mg BID on an AUC basis.

14 CLINICAL STUDIES

14.1 Clinical Trials in Pulmonary Arterial Hypertension

Four multicenter, randomized, double-blind studies were conducted and compared Orenitram to placebo in a total of 349 (Study 1), 350 (Study 2), 310 (Study 3), and 690 (Study 4) patients with PAH.

Study 1 (effect seen with no background vasodilator)

Study 1 was a 12-week, randomized (2:1 Orenitram to placebo), double-blind, placebo-controlled, international efficacy and safety study of Orenitram in patients with WHO Group 1 PAH not currently receiving PAH therapy. The primary efficacy endpoint was placebo-corrected change in six-minute walk distance (6MWD) from Baseline to Week 12. Study drug dose was titrated to a maximum of 12 mg BID based on clinical response and study drug tolerability. Study 1 enrolled 349 patients (overall analysis population) who were not receiving any PAH medication. At the beginning of the study, subjects were dosed with only the 1 mg tablets with 0.5 and 0.25 mg tablets introduced at sequentially later dates during the study. The primary analysis population consisted of the 228 patients who had access to the 0.25 mg tablet at the time of randomization. Patients were administered Orenitram or placebo twice daily, with the doses titrated to effect over the course of the 12-week trial. Patients were in WHO functional class II (~33%) and class III (~66%) with either idiopathic or heritable PAH (~75%), collagen vascular disease associated PAH (~19%), or PAH associated with HIV (1%) or congenital heart defect (5%) or other conditions (~6%). The patients' mean baseline 6MWD was approximately 330 meters. In the primary analysis population, 17% of patients discontinued Orenitram compared to 14% of patients on placebo.

The primary efficacy endpoint of the trial was the change in 6MWD at 12 weeks for the primary analysis population. Analysis of Study 1 results demonstrated that those patients receiving Orenitram compared to patients receiving placebo improved their median change in 6MWD by approximately 23 meters (p=0.013) as compared to patients receiving placebo as demonstrated in (Figure 2). The within group median change from baseline was +25 meters for Orenitram and -5 meters for placebo at Week 12 (N=228). Mean dose (±SD) in the Orenitram group was 2.3 ± 1.3, 3.2 ± 1.9, and 3.4 ± 1.9 mg BID at Weeks 4, 8, and 12, respectively, with a maximum dose of 12 mg BID. The distribution of the 6MWD change from baseline at Week 12 was also plotted across the range of observed values (Figure 3).

Figure 2: Estimate of Treatment Effect by Visit for the Primary Analysis Population (Study 1)

Figure 3: Plot of the Distribution of Peak 6MWD Changes at Week 12 for the Primary Analysis Population (Study 1)

The placebo-corrected median treatment effect on 6MWD was estimated within various subpopulations defined by age, gender, disease etiology, and baseline 6MWD (Figure 4).

Figure 4: Placebo Corrected Median Treatment Effect (with 95% CI) on 6MWD Change from Baseline at Week 12 for Various Subgroups in the Primary Analysis Population (Study 1)

Studies 2 and 3 (no effect on a background of ERA, PDE-5 inhibitor, or both)

Studies 2 (N=350) and 3 (N=310) were 16-week, randomized, double-blind, placebo-controlled, international efficacy and safety studies of Orenitram in patients with WHO Group 1 PAH. The primary efficacy endpoint was placebo-corrected change in 6MWD from Baseline to Week 16. Patients were in WHO functional class II (~23%) and class III (~77%) with either idiopathic or heritable PAH (~66%), collagen vascular disease associated PAH (~29%), or PAH associated with HIV (1%) or congenital heart defect (4%). The patients' mean baseline 6MWD was approximately 340 meters. Approximately 40% were receiving both an ERA and a PDE-5 inhibitor. The results did not demonstrate a benefit in exercise testing with median 6MWD at Week 16.

Study 4 (effect seen with a single background PAH therapy)

The effect of Orenitram on the progression of PAH was demonstrated in an international, multicenter, double-blind, event-driven study in patients with WHO Group 1 PAH randomized 1:1 to Orenitram or placebo (Study 4). The primary efficacy endpoint was the time to first clinical worsening (morbidity or mortality) event. Study drug dose was titrated starting at 0.125 mg TID to a maximum of 12 mg TID based on clinical response and study drug tolerability. Study 4 enrolled a total of 690 patients (primary efficacy analysis population) who were currently receiving a single approved PAH therapy (PDE-5 inhibitor or soluble guanylate cyclase (sGC) [72%]; ERA [28%]). The median age was 43 years and most patients were white (52%) and female (79%). The majority of patients were lower risk in WHO functional class II (63%) with a mean (±SD) baseline 6MWD of 396 (±96) meters. Most patients had either idiopathic or heritable PAH (63%) or collagen vascular disease associated PAH (26%).

Patients treated with Orenitram achieved a median dose of 3.6 mg TID at Week 24, which continued to increase until approximately Week 60 where the median dose of Orenitram was approximately 5 mg TID.

Treatment with Orenitram resulted in a significant increase in the time to first clinical worsening event compared with patients who received placebo, which was associated with a reduction in the risk of an event (HR=0.75 [95% CI; 0.57, 0.99]; p=0.039; Figure 5). The beneficial effect of Orenitram was primarily attributable to a delay in disease progression—defined as a 15% decline in 6MWD plus an increase in either WHO Functional Class or worsening of signs or symptoms of right heart failure—(HR=0.39 [95% CI; 0.23, 0.66]; Figure 6), but there was no effect on the other components of clinical worsening (Table 2).

Figure 5: Kaplan-Meier Plot of Time to Clinical Worsening Events for the Primary Analysis Population (Study 4)

Table 2: Primary Endpoint Events (Study 4)
 |  |  | Orenitram % N=346 | Placebo % N=344 | HR (95% CI)
Clinical worsening |  |  | 26 | 36 | 0.75 (0.57, 0.99)
Any of these | All-cause mortality |  | 4.3 | 4.1
Any of these | Hospitalization for PAH |  | 10 | 10
Any of these | Inhaled/IV PGI2 |  | 0.6 | 1.5
Any of these | Unsatisfactory long-term clinical response |  | 5.5 | 5.8
Any of these | Disease progression |  | 5.5 | 14.5 | 0.39 (0.23, 0.66)
 | This → | 15% decrease in 6MWD | 5.5 | 14.5
 | Plus one of these | Increase in WHO functional class | 2.6 | 8.1
 |  | Increased RHF symptoms | 2.9 | 6.4
6MWD, 6-minute walk distance; CI, confidence interval; HR, hazard ratio; IV PGI2, intravenously administered prostacyclin; PAH, pulmonary arterial hypertension; RHF, right heart failure; WHO, World Health Organization

Figure 6: Kaplan-Meier Plot of Time to Disease Progression for the Primary Analysis Population (Study 4)

The treatment effect on time to first clinical worsening event due to disease progression was consistent for various subgroups defined by age, sex, baseline 6MWD, WHO functional class, disease etiology, geographical regions, and background therapy (Figure 7).

Figure 7: Forest Plot of Subgroup Analyses of Time to Disease Progression for Various Subgroups in the Primary Analysis Population (Study 4)

Long-Term Treatment of Pulmonary Arterial Hypertension

Patients (N=824) from the placebo-controlled studies entered a long-term, uncontrolled, open-label extension study. The average exposure to Orenitram was approximately 2 years with a maximum exposure of approximately 6 years. The dose of Orenitram continued to increase over time with doses (mean ± SD) of 3.6 ± 2.7, 4.2 ± 3.1, and 5 ± 3.7 mg BID at 6 (n=649), 12 (n=433), and 24 months (n=238), respectively, with a maximum dose of 21 mg BID. Reasons for discontinuation from the study included adverse event (16%), progression of disease (15%), death (13%), and withdrawn consent (7%). In the 522 subjects that completed the 12-month efficacy assessment, their mean 6MWD improved by 24 meters compared to baseline (30 meters in monotherapy patients and 20 meters when Orenitram was used in combination with an ERA and/or a PDE-5 inhibitor). Of the patients that remained in the study, overall survival was 92%, 87%, and 82% at the end of 1, 2, and 3 years, respectively, with progression-free survival (progression defined as death, discontinuation, or addition of a PAH therapy) of 74%, 61%, and 47%. Without a control group, these data must be interpreted cautiously.

Remodulin to Orenitram Transition Study

A 24-week, multicenter, open-label study enrolled 33 WHO Group 1 patients on stable doses of Remodulin. All patients received background therapy with a PDE-5 inhibitor and/or ERA. Patients were WHO functional class I or II and hemodynamically stable at baseline with a cardiac index >2.2 L/m^2, RAP <11 mmHg, and PVR <10 Wood units. The primary endpoint of the study was the safety and tolerability of the transition. Successful transition was defined as transition from Remodulin to Orenitram at Week 4 (no longer receiving Remodulin) and clinically maintained on Orenitram through Week 24 (as measured by 6MWD and hemodynamics).

All patients transitioned from Remodulin to Orenitram (median time to transition of 3 days) with thirty-one patients (94%) completing transition in 5 days (range 2 to 29 days). Two subjects discontinued Orenitram. After 24 weeks of treatment with Orenitram, 6MWD and hemodynamics remained stable. Without a control group, these data must be interpreted cautiously.

16 HOW SUPPLIED/STORAGE AND HANDLING

16.1 How Supplied

Orenitram is an 8-mm round biconvex tablet with strength identified by color and print and supplied as follows:

Strength | Color | Printing on Tablets | NDC # 100-Count Bottle | NDC # 10-Count Bottle | NDC # 10-Count Carton (Unit-Dose Blister)
0.125 mg | White | UT 0.125 | 66302-300-01 | 66302-300-10 | 66302-300-02
0.25 mg | Green | UT 0.25 | 66302-302-01 | 66302-302-10 | 66302-302-02
1 mg | Yellow | UT 1 | 66302-310-01 | 66302-310-10 | 66302-310-02
2.5 mg | Pink | UT 2.5 | 66302-325-01 | 66302-325-10 | 66302-325-02
5 mg | Red | UT 5 | 66302-350-01 | 66302-350-10 | 66302-350-02

Titration Kits for Orenitram are supplied in the following configurations:

Titration Kit | Blister Configurations | NDC #
Month 1 containing four weekly cartons | Seven daily wallet blister packs in each weekly carton containing the following total number of tablets:; - Week 1 (twenty-one × 0.125 mg tablets) - Week 2 (forty-two × 0.125 mg tablets) - Week 3 (twenty-one × 0.125 mg tablets and twenty-one × 0.25 mg tablets) - Week 4 (forty-two × 0.125 mg tablets and twenty-one × 0.25 mg tablets) | 66302-361-28
Month 2 containing four weekly cartons | Seven daily wallet blister packs in each weekly carton containing the following total number of tablets:; - Week 5 (twenty-one × 0.125 mg tablets and forty-two × 0.25 mg tablets) - Week 6 (forty-two × 0.125 mg tablets and forty-two × 0.25 mg tablets) - Week 7 (twenty-one × 0.125 mg tablets and sixty-three × 0.25 mg tablets) - Week 8 (forty-two × 0.125 mg tablets and sixty-three × 0.25 mg tablets) | 66302-362-56
Month 3 containing four weekly cartons | Seven daily wallet blister packs in each weekly carton containing the following total number of tablets:; - Week 9 (twenty-one × 0.125 mg tablets and twenty-one × 1 mg tablets) - Week 10 (forty-two × 0.125 mg tablets and twenty-one × 1 mg tablets) - Week 11 (twenty-one × 0.125 mg tablets, twenty-one × 0.25 mg tablets, and twenty-one × 1 mg tablets) - Week 12 (forty-two × 0.125 mg tablets, twenty-one × 0.25 mg tablets, and twenty-one × 1 mg tablets) | 66302-363-84

16.2 Storage

Store at 20°C to 25°C (68°F to 77°F) with excursions permitted to 15°C to 30°C (59°F to 86°F) [See USP Controlled Room Temperature]. Keep out of reach of children.

17 PATIENT COUNSELING INFORMATION

See FDA-approved patient labeling (Patient Information).

Tell patients:

- Abrupt discontinuation of therapy could result in worsening of PAH symptoms.
- Take Orenitram with food.
- Swallow Orenitram tablets whole. Do not split, chew, crush, or break. Do not take a tablet that is damaged or broken.
- The biologically inert components of the tablet remain intact during gastrointestinal transit and are eliminated in the feces as an insoluble shell.

©Copyright 2023 United Therapeutics Corp. All rights reserved.

United Therapeutics Corp.
Research Triangle Park, NC 27709

Patient Information
Orenitram(®) (oh-REN-i-tram)
(treprostinil) extended-release tablets

What is Orenitram?

- Orenitram is a prescription medicine used to treat pulmonary arterial hypertension (PAH) which is high blood pressure in the arteries of your lungs.
- Orenitram can help slow down the progression of your disease and improve your ability to exercise.

It is not known if Orenitram is safe and effective in children.

Do not take Orenitram if you have severe liver problems.

Before taking Orenitram, tell your healthcare provider about all of your medical conditions, including if you:

- have liver problems
- have diverticulosis
- are pregnant or plan to become pregnant. It is not known if Orenitram will harm your unborn baby.
- are breastfeeding or plan to breastfeed. It is not known if Orenitram passes into your breast milk. Talk to your healthcare provider about the best way to feed your baby during treatment with Orenitram.

Tell your healthcare provider about all the medicines you take, including prescription and over-the-counter medicines, vitamins, and herbal supplements. Orenitram and other medicines may affect each other causing side effects. Do not start any new medicine until you check with your healthcare provider.
Especially tell your healthcare provider if you take another medicine that contains treprostinil, such as Remodulin®, Tyvaso®, or Tyvaso DPI®.

How should I take Orenitram?

- Take Orenitram exactly as your healthcare provider tells you to take it.
- Your healthcare provider will slowly increase your dose to find the dose of Orenitram that is right for you.
- If you take the medicine Remodulin and your healthcare provider is switching you to Orenitram, your healthcare provider will decrease your dose of Remodulin over a period of time when you start taking Orenitram.
- Do not change your dose or suddenly stop taking Orenitram without first talking to your healthcare provider.
- Orenitram is usually taken 3 times a day (about every 8 hours) or 2 times a day (about every 12 hours). Your healthcare provider will tell you how often you should take Orenitram. If you have side effects, your healthcare provider may tell you to change your dose or when you take Orenitram.
- Take Orenitram with food.
- Swallow Orenitram tablets whole. Do not split, chew, crush, or break your Orenitram tablets. Do not take Orenitram tablets that are damaged or broken. If Orenitram tablets are not taken whole, they may release too much medicine at one time. This can lead to side effects.
- You may see the tablet shell in your stools (bowel movements). This is usually normal. The tablet shell is not digested. If you have diverticulosis, the tablet shell may get stuck in a blind pouch or diverticulum in your intestine.
- If you miss your dose of Orenitram, take the missed dose as soon as possible with food.
- If you miss 2 or more doses of Orenitram, call your healthcare provider to see if you need to change your dose.
- If you take too much Orenitram, call your healthcare provider or go to the nearest hospital emergency room right away.

What are the possible side effects of Orenitram?
Orenitram can cause serious side effects, including worsening of PAH symptoms.

- Stopping Orenitram suddenly may cause worsening of your PAH symptoms. Do not change your dose or suddenly stop taking Orenitram without first talking to your healthcare provider.

The most common side effects of Orenitram include:

- headache
- diarrhea
- nausea
- vomiting

- flushing
- pain in arms and legs
- jaw pain

Tell your healthcare provider if you have any side effect that bothers you or that does not go away.
These are not all of the possible side effects of Orenitram. For more information, ask your healthcare provider or pharmacist.
Call your healthcare provider for medical advice about side effects. You may report side effects to FDA at 1-800-FDA-1088.

How should I store Orenitram?

- Store at 68°F to 77°F (20°C to 25°C).

Keep Orenitram and all medicines out of the reach of children.

General information about the safe and effective use of Orenitram.
Medicines are sometimes prescribed for purposes other than those listed in a Patient Information Leaflet.
Do not use Orenitram for a condition for which it was not prescribed. Do not give Orenitram to other people, even if they have the same symptoms that you have. It may harm them. You can ask your healthcare provider or pharmacist for information about Orenitram that is written for health professionals.

What are the ingredients in Orenitram?
Active ingredient: treprostinil diolamine
Inactive ingredients: xylitol, maltodextrin, sodium lauryl sulfate, magnesium stearate, cellulose acetate, triethyl citrate, polyvinyl alcohol, titanium dioxide, polyethylene glycol, and talc. In addition, tablets may contain colorants FD&C Blue #2, iron oxide yellow, and iron oxide red. The imprint ink contains shellac glaze, ethanol, isopropyl alcohol, iron oxide black, n-butyl alcohol, and propylene glycol.
United Therapeutics Corp., Research Triangle Park, NC 27709 USA
Copyright 2023, United Therapeutics Corp. All rights reserved.
ORENITRAM is a registered trademark of United Therapeutics Corp.
For more information, go to www.orenitram.com or call 1-877-864-8437.

This Patient Information has been approved by the U.S. Food and Drug Administration.

Revised: 02/2023

PRINCIPAL DISPLAY PANEL - 0.125 mg Tablet Bottle Label

NDC 66302-300-01

100 Tablets

Orenitram®
(treprostinil)
Extended-Release
Tablets

0.125 mg

Swallow whole.
Do not split, chew, crush,
or break tablets.

PRINCIPAL DISPLAY PANEL - 0.125 mg Tablet Blister Pack Carton

Orenitram®
(treprostinil)
EXTENDED-RELEASE TABLETS

0.125 mg
per tablet

Swallow whole.
Do not split, chew,
crush, or break tablets.

10 Tablets
(1 x 10 tablet blister pack)

Pharmacist:
Dispense the accompanying Patient
Information Leaflet to each patient.

Rx Only
NDC 66302-300-02

PRINCIPAL DISPLAY PANEL - 0.25 mg Tablet Bottle Label

NDC 66302-302-01

100 Tablets

Orenitram®
(treprostinil)
Extended-Release
Tablets

0.25 mg

Swallow whole.
Do not split, chew, crush,
or break tablets.

PRINCIPAL DISPLAY PANEL - 0.25 mg Tablet Blister Pack Carton

Orenitram®
(treprostinil)
EXTENDED-RELEASE TABLETS

0.25 mg
per tablet

Swallow whole.
Do not split, chew,
crush, or break tablets.

10 Tablets
(1 x 10 tablet blister pack)

Pharmacist:
Dispense the accompanying Patient
Information Leaflet to each patient.

Rx Only
NDC 66302-302-02

PRINCIPAL DISPLAY PANEL - 1 mg Tablet Bottle Label

NDC 66302-310-01

100 Tablets

Orenitram®
(treprostinil)
Extended-Release
Tablets

1 mg

Swallow whole.
Do not split, chew, crush,
or break tablets.

PRINCIPAL DISPLAY PANEL - 1 mg Tablet Blister Pack Carton

Orenitram®
(treprostinil)
EXTENDED-RELEASE TABLETS

1 mg
per tablet

Swallow whole.
Do not split, chew,
crush, or break tablets.

10 Tablets
(1 x 10 tablet blister pack)

Pharmacist:
Dispense the accompanying Patient
Information Leaflet to each patient.

Rx Only
NDC 66302-310-02

PRINCIPAL DISPLAY PANEL - 2.5 mg Tablet Bottle Label

NDC 66302-325-01

100 Tablets

Orenitram®
(treprostinil)
Extended-Release
Tablets

2.5 mg

Swallow whole.
Do not split, chew, crush,
or break tablets.

PRINCIPAL DISPLAY PANEL - 2.5 mg Tablet Blister Pack Carton

Orenitram®
(treprostinil)
EXTENDED-RELEASE TABLETS

2.5 mg
per tablet

Swallow whole.
Do not split, chew,
crush, or break tablets.

10 Tablets
(1 x 10 tablet blister pack)

Pharmacist:
Dispense the accompanying Patient
Information Leaflet to each patient.

Rx Only
NDC 66302-325-02

PRINCIPAL DISPLAY PANEL - 5 mg Tablet Bottle Label

NDC 66302-350-01

100 Tablets

Orenitram®
(treprostinil)
Extended-Release
Tablets

5 mg

Swallow whole.
Do not split, chew, crush,
or break tablets.

PRINCIPAL DISPLAY PANEL - 5 mg Tablet Blister Pack Carton

Orenitram®
(treprostinil)
EXTENDED-RELEASE TABLETS

5 mg
per tablet

Swallow whole.
Do not split, chew,
crush, or break tablets.

10 Tablets
(1 x 10 tablet blister pack)

Pharmacist:
Dispense the accompanying Patient
Information Leaflet to each patient.

Rx Only
NDC 66302-350-02

PRINCIPAL DISPLAY PANEL - 0.125 mg 0.25 mg Titration Kit Carton - Month 1

Rx Only

NDC 66302-361-28

Orenitram®
(treprostinil)
EXTENDED-RELEASE TABLETS

Titration Kit

Month 1

0.125 mg
per tablet

0.25 mg
per tablet

Swallow whole.
Do not split, chew, crush, or break tablets.

Kit Contains:
168 tablets (126 x 0.125 mg per tablet and
42 x 0.25 mg per tablet).
Monthly carton contains 4 individual weekly cartons
each with 7 daily wallet blister packs.

PRINCIPAL DISPLAY PANEL - 0.125 mg 0.25 mg Titration Kit Carton - Month 2

Rx Only

NDC 66302-362-56

Orenitram®
(treprostinil)
EXTENDED-RELEASE TABLETS

Titration Kit

Month 2

0.125 mg
per tablet

0.25 mg
per tablet

Swallow whole.
Do not split, chew, crush, or break tablets.

Kit Contains:
336 tablets (126 x 0.125 mg per tablet and
210 x 0.25 mg per tablet).
Monthly carton contains 4 individual weekly cartons
each with 7 daily wallet blister packs.

PRINCIPAL DISPLAY PANEL - 0.125 mg 0.25 mg 1 mg Titration Kit Carton - Month 3

Rx Only

NDC 66302-363-84

Orenitram®
(treprostinil)
EXTENDED-RELEASE TABLETS

Titration Kit

Month 3

0.125 mg
per tablet

0.25 mg
per tablet

1 mg
per tablet

Swallow whole.
Do not split, chew, crush, or break tablets.

Kit Contains:
252 tablets (126 x 0.125 mg per tablet,
42 x 0.25 mg per tablet, and 84 × 1 mg per tablet).
Monthly carton contains 4 individual weekly cartons
each with 7 daily wallet blister packs.